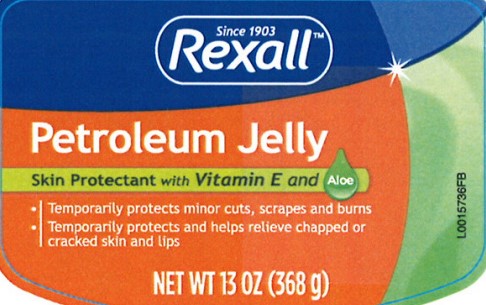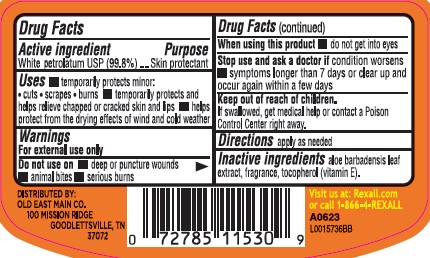 DRUG LABEL: Petroleum
NDC: 55910-235 | Form: JELLY
Manufacturer: Old East Main Co.
Category: otc | Type: HUMAN OTC DRUG LABEL
Date: 20260302

ACTIVE INGREDIENTS: PETROLATUM 998 mg/1 g
INACTIVE INGREDIENTS: ALOE VERA LEAF; TOCOPHEROL

Rexall 235.002/235AC
Petroleum Jelly

Active ingredient

White petrolatum USP (99.8%)

Purpose

Skin protectant

Use

- temporarily protects minor: •cuts •scrapes •burns
- temporarily protects and helps relieve chapped or cracked skin and lips
- helps protect from the drying effects of wind and cold weather

Warnings

For external use only

Do not use

- deep or puncture wounds
- animal bite
- serious burns

When using this product

- do not get into eyes

Stop use and ask a doctor if condition worsens

- symptoms longer than 7 days or clear up and occur again with in a few days

Keep out of reach of children.

If swallowed, get medical help or contact a Poison Control Center right away.

directions

- apply as needed

Inactive ingredients

aloe barbadensis leaf extract, fragrance, tocopherol (vitamin E)

ADVERSE REACTION

DISTRIBUTED BY:

OLD EAST MAIN CO.

100 MISSION RIDGE

GOODLETTSVILLE, TN 37072

Visit us at: Rexall.com or call 1-866-4-REXALL

principal display panel

Since 1903

Rexall™

Petroleum Jelly

Skin Protectant with Vitamin E and Aloe

- Temporarily protects minor cuts, scrapes and burns
- Temporarily protects and helps relieve chapped or cracked skin and lips

NET WT 13 OZ (368 g)